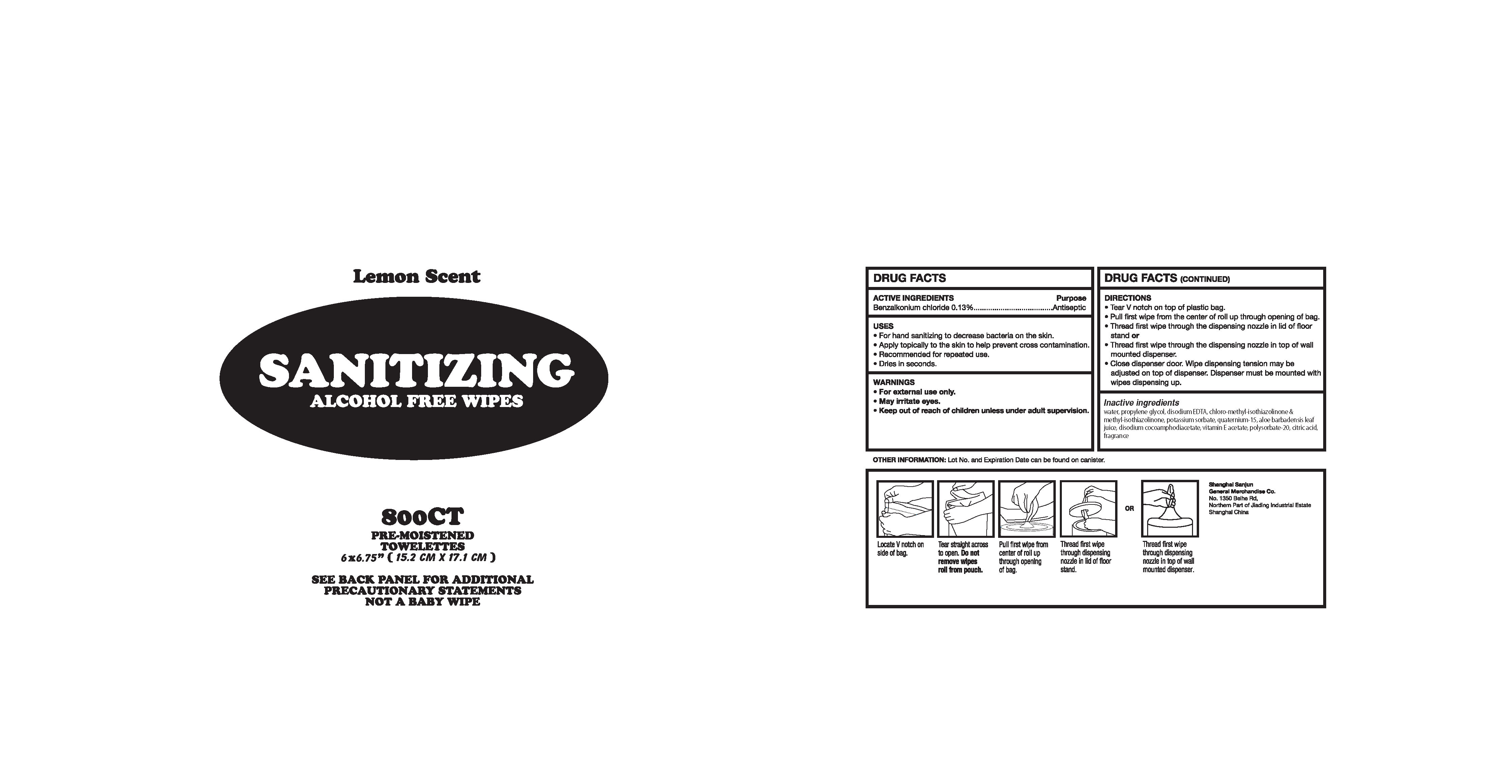 DRUG LABEL: Alcohol-free Hand sanitizing wipes 800CT
NDC: 75670-005 | Form: CLOTH
Manufacturer: SHANGHAI SANJUN GENERAL MERCHANDISE CO., LTD.
Category: otc | Type: HUMAN OTC DRUG LABEL
Date: 20220224

ACTIVE INGREDIENTS: BENZALKONIUM CHLORIDE 0.1 g/100 g
INACTIVE INGREDIENTS: QUATERNIUM-15; WATER; POTASSIUM SORBATE; METHYLCHLOROISOTHIAZOLINONE; PROPYLENE GLYCOL; METHYLISOTHIAZOLINONE; CITRIC ACID MONOHYDRATE; ALOE VERA FLOWER; ALPHA-TOCOPHEROL ACETATE; DISODIUM COCOAMPHODIACETATE; POLYSORBATE 20; EDETATE DISODIUM ANHYDROUS

75670-005 Alcohol-free Hand sanitizing wipes 800CT 0.13%Benzalkonium Chloride

Active Ingredient

Benzalkonium Chloride 0. 13 %

PURPOSE

Antiseptic

USE

●For hand sanitizing to decrease bacteria on the skin.
●Apply topically to the skin to help prevent cross contamination.
●Recommended for repeated use.
Dries in seconds.

Warning

●For extemal use only
●May iritate eyes

Keep out of reach of children unless under
adult supervision

Directions

●Tear V notch on top of plastic bag.
●Pull first wipe from the center of roll up through opening of bag.
●Thread first wipe through the dispensing nozzle in lid of floor
stand or
●Thread first wipe through the dispensing nozzle in top of wall
mounted dispenser.
●Close dispenser door. Wipe dispensing tension may be
adjusted on top of dispenser. Dispenser must be mounted with
wipes dispensing up.

Inactive ingredients

water, propylene glycol, disodium EDTA, chloro-methyl-isothiazolinone &
methyl-isothiazolinone, potassium sorbate, quaternium-15, aloe barbadensis leaf
juice, disodium cocoamphodiacetate, vitamin E acetate, polysorbate: 20, citric acid,
fragrance